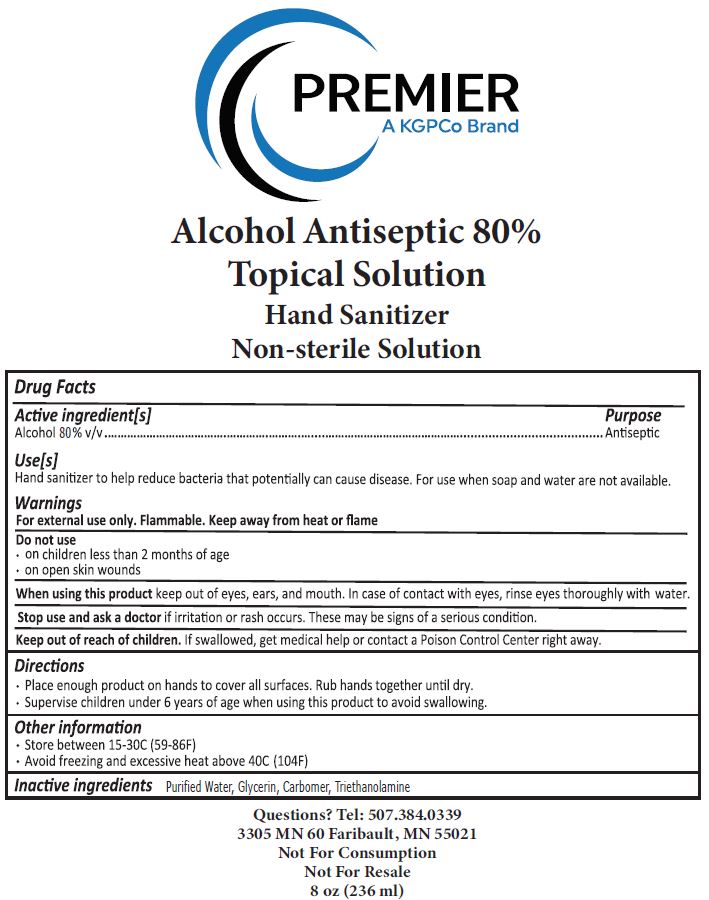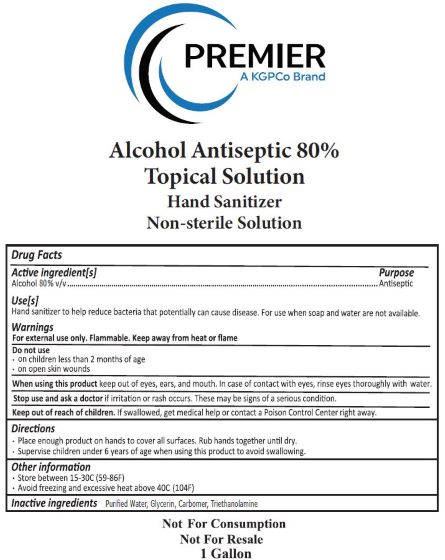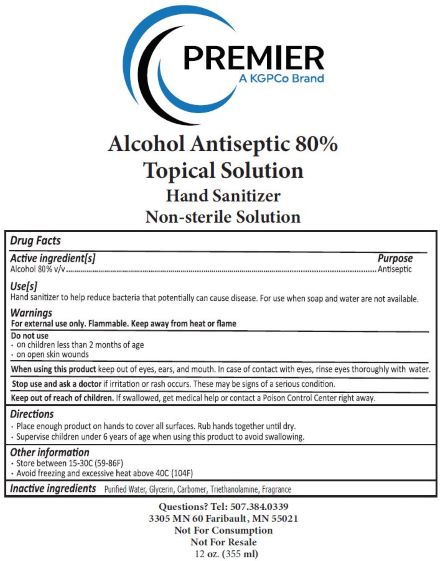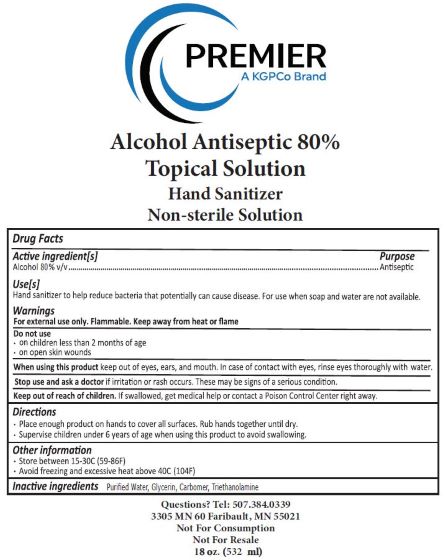 DRUG LABEL: Hand Sanitizer
NDC: 73874-0002 | Form: LIQUID
Manufacturer: Elevation Gourmet, Inc.
Category: otc | Type: HUMAN OTC DRUG LABEL
Date: 20200812

ACTIVE INGREDIENTS: ALCOHOL 80.02 mL/100 mL
INACTIVE INGREDIENTS: WATER 18.5 mL/100 mL; CARBOMER 940 0.92 mL/100 mL; GLYCEROL FORMAL 0.0068267 mL/100 mL; TROLAMINE 0.35 mL/100 mL

Active Ingredient(s)

Alcohol 80% v/v

PURPOSE

Use(s)

Hand sanitizer to help reduce bacteria that potentially can cause disease. For use when soap and Water are not available.

Warnings

For external use only. Flammable. Keep way from heat or flame

Do Not Use

- on children less than 2 months of age
- on open skin wounds

When using this product keep out of eyes, ears, and mouth. In case of contact wth eyes, rinse eyes thoroughly with water.

Stop use and ask a doctor if irritation or rash occurs. These may be sign of a serious condition.

Keep out of reach of children. If swallowed, get medical help or contract a Poison Control Center right away.

Directions

- Place enought product on hands to cover all surfaces. Rub hands together until dry.
- Supervise children under 6 years of age when using this product to avoid swallowing.

Other information

- Store between 15-30C (59-86F)
- Avoid freezing and excessive heat above 40C (104F)

INACTIVE INGREDIENT

Inactive ingredients Purified Water, Glyderin, Carbomer, Triethanolamine

Directions

- Place enough product on hands to cover all surfaces. Rub hands together until dry.
- Supervise children under 6 years of age when using this product to avoid swallowing.

INDICATIONS AND USAGE

Use(s)

Hand sanitizer to help reduce bacteria that potentially can cause disease. For use when soap and water are not available.

Directions

- Place enough product on hands to cover all surfaces. Rub hand togetherr until dry.
- Supervise children under 6 years of age when using this product to avoid swallowing.

PACKAGE LABEL

8 oz 73874-0002-1

PACKAGE LABEL

12oz 73874-0002-2

PACKAGE LABEL

18 oz 73874-0002-3

PACKAGE LABEL

1 gal 73874-0002-4